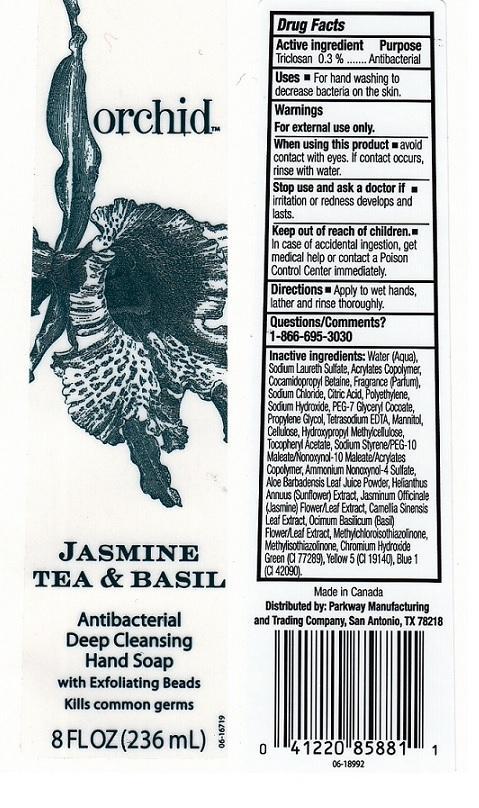 DRUG LABEL: ORCHID
NDC: 37808-090 | Form: LIQUID
Manufacturer: H.E.B.
Category: otc | Type: HUMAN OTC DRUG LABEL
Date: 20130813

ACTIVE INGREDIENTS: TRICLOSAN 3 mg/1 mL
INACTIVE INGREDIENTS: WATER; SODIUM LAURETH SULFATE; METHACRYLIC ACID - METHYL METHACRYLATE COPOLYMER (1:1); COCAMIDOPROPYL BETAINE; SODIUM CHLORIDE; CITRIC ACID MONOHYDRATE; HIGH DENSITY POLYETHYLENE; SODIUM HYDROXIDE; PEG-7 GLYCERYL COCOATE; PROPYLENE GLYCOL; EDETATE SODIUM; MANNITOL; POWDERED CELLULOSE; HYPROMELLOSES; .ALPHA.-TOCOPHEROL ACETATE; AMMONIUM NONOXYNOL-4 SULFATE; ALOE VERA LEAF; HELIANTHUS ANNUUS FLOWERING TOP; JASMINUM OFFICINALE FLOWER; GREEN TEA LEAF; OCIMUM BASILICUM FLOWERING TOP; METHYLCHLOROISOTHIAZOLINONE; METHYLISOTHIAZOLINONE; CHROMIUM HYDROXIDE GREEN; FD&C YELLOW NO. 5; FD&C BLUE NO. 1

DRUG FACTS

ACTIVE INGREDIENT

TRICLOSAN 0.3%

PURPOSE

ANTIBACTERIAL

USES

FOR HAND WASHING TO DECREASE BACTERIA ON THE SKIN.

WARNINGS

FOR EXTERNAL USE ONLY.

WHEN USING THIS PRODUCT

AVOID CONTACT WITH EYES. IF CONTACT OCCURS, RINSE WITH WATER.

STOP USE AND ASK A DOCTOR IF

IRRITATION OR REDNESS DEVELOPS AND LASTS.

KEEP OUT OF REACH OF CHILDREN

IN CASE OF ACCIDENTAL INGESTION, GET MEDICAL HELP OR CONTACT A POISON CONTROL CENTER IMMEDIATELY.

DIRECTIONS

APPLY TO WET HANDS, LATHER AND RINSE THOROUGHLY.

QUESTIONS/COMMENTS?

1-866-695-3030

INACTIVE INGREDIENTS:

WATER (AQUA), SODIUM LAURETH SULFATE, ACRYLATES COPOLYMER, COCAMIDOPROPYL BETAINE, FRAGRANCE (pARFUM), SODIUM CHLORIDE, CITRIC ACID, POLYETHYLENE, SODIUM HYDROXIDE, PEG-7 GLYCERYL COCOATE, PROPYLENE GLYCOL, TETRASODIUM EDTA, MANNITOL, CELLULOSE, HYDROXYPROPYL METHYLCELLULOSE, TOCOPHERYL ACETATE, SODIUM STYRENE/PEG-10 MALEATE/NONOXYNOL-10 MALEATE/ACRYLATES COPOLYMER, AMMONIUM NONOXYNOL-4 SULFATE, ALOE BARBADENSIS LEAF JUICE POWDER, HELIANTHUS ANNUUS (SUNFLOWER) EXTRACT, JASMINUM OFFICINALE (JASMINE) FLOWER/LEAF EXTRACT, CAMELLIA SINENSIS LEAF EXTRACT, OCIMUM BASILICUM (BASIL) FLOWER/LEAF EXTRACT, METHYLCHLOROISOTHIAZOLINONE, METHYLISOTHIAZOLINONE, CHROMIUM HYDROXIDE GREEN (CI 77289), YELLOW 5 (CI 19140), BLUE 1 (CI 42090).